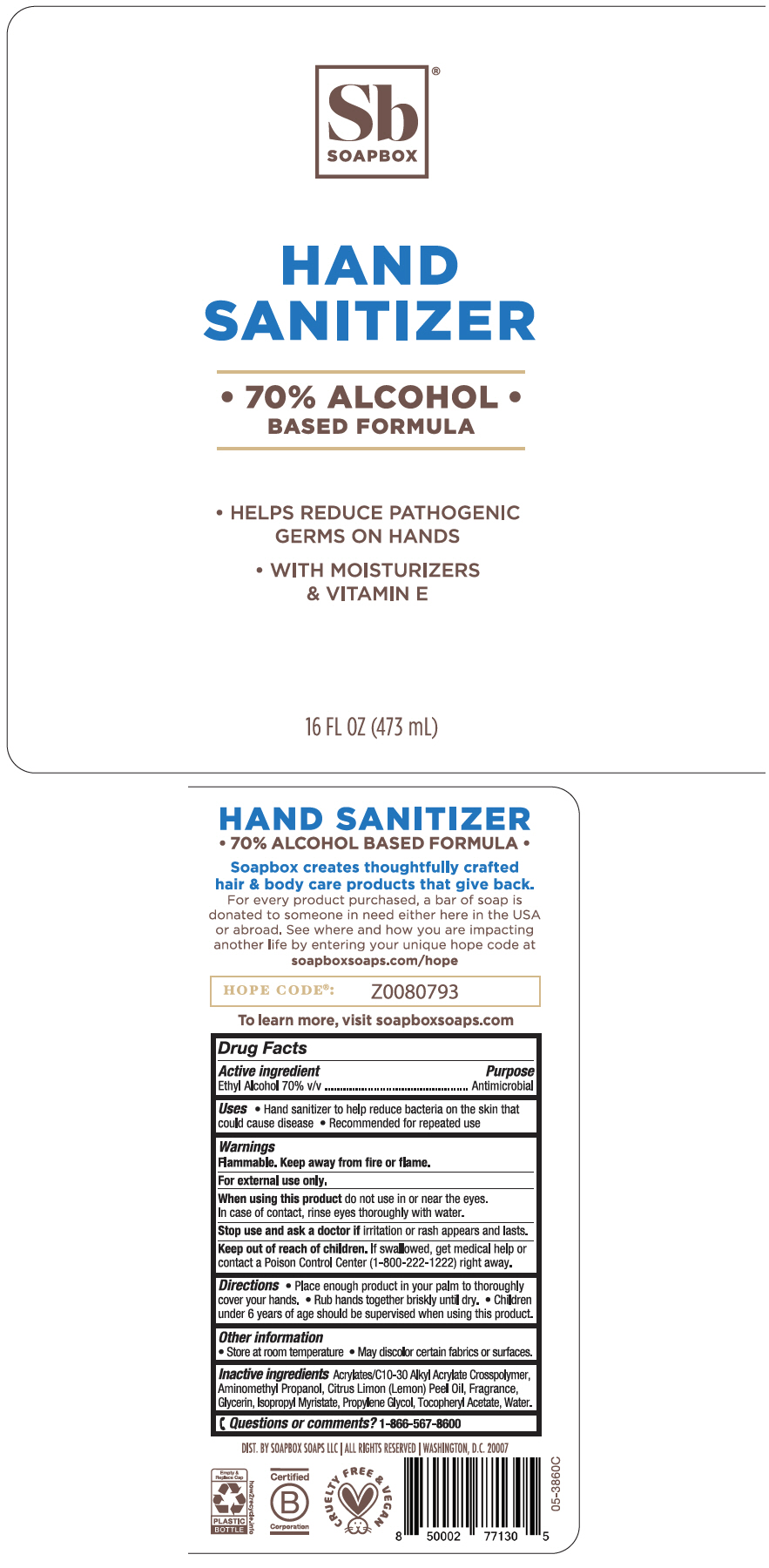 DRUG LABEL: Soapbox Hand Sanitizer 
NDC: 75115-306 | Form: GEL
Manufacturer: Soapbox Soaps, LLC
Category: otc | Type: HUMAN OTC DRUG LABEL
Date: 20200707

ACTIVE INGREDIENTS: Alcohol 700 mg/1 mL
INACTIVE INGREDIENTS: CARBOMER INTERPOLYMER TYPE A (ALLYL SUCROSE CROSSLINKED); AMINOMETHYLPROPANOL; LEMON OIL; Glycerin; Isopropyl Myristate; Propylene Glycol; .ALPHA.-TOCOPHEROL ACETATE, DL-; Water

Soap Box® Hand Sanitizer

Drug Facts

Active ingredient

Ethyl Alcohol 70% v/v

Purpose

Antimicrobial

Uses

⬥ Hand sanitizer to help reduce bacteria on the skin that could cause disease
⬥ Recommended for repeated use

Warnings

Flammable. Keep away from fire or flame.

For external use only.

When using this product do not use in or near the eyes. In case of contact, rinse eyes thoroughly with water.

Stop use and ask a doctor if irritation or rash appears and lasts..

Keep out of reach of children. If swallowed, get medical help or contact a Poison Control Center (1-800-222-1222) right away.

Directions

⬥ place enough product in your palm to thoroughly cover your hands
⬥ Rub hands together briskly until dry.
⬥ Children under 6 years of age should be supervised when using this product.

Other information

⬥ Store at room temperature
⬥ May discolor certain fabrics or surfaces.

Inactive ingredients

Acrylates/C10-30 Alkyl Acrylate Crosspolymer, Aminomethyl Propanol, Citrus Limon (Lemon) Peel Oil, Fragrance, Glycerin, Isopropyl Myristate, Propylene Glycol, Tocopheryl Acetate, Water

Questions or comments?

1-866-567-8600

DIST. BY SOAPBOX SOAPS LLC | ALL RIGHTS RESERVED | WASHINGTON, D.C. 20007

PRINCIPAL DISPLAY PANEL - 473 mL Bottle Label

Sb®
SOAPBOX

HAND
SANITIZER

• 70% ALCOHOL •
BASED FORMULA

• HELPS REDUCE PATHOGENIC
GERMS ON HANDS

• WITH MOISTURIZERS
& VITAMIN E

16 FL OZ (473 mL)